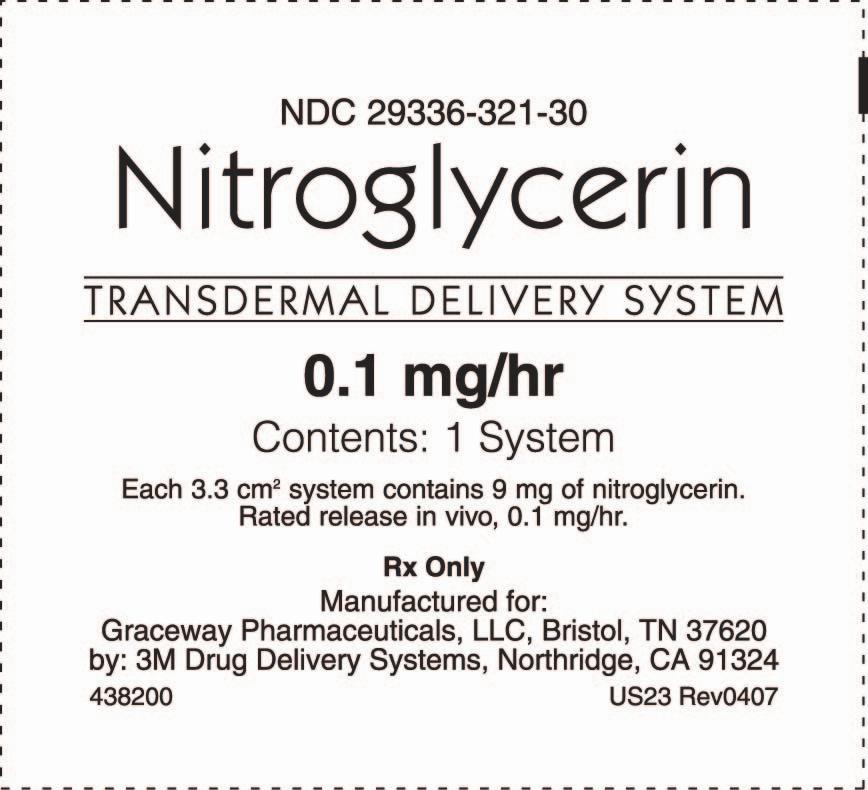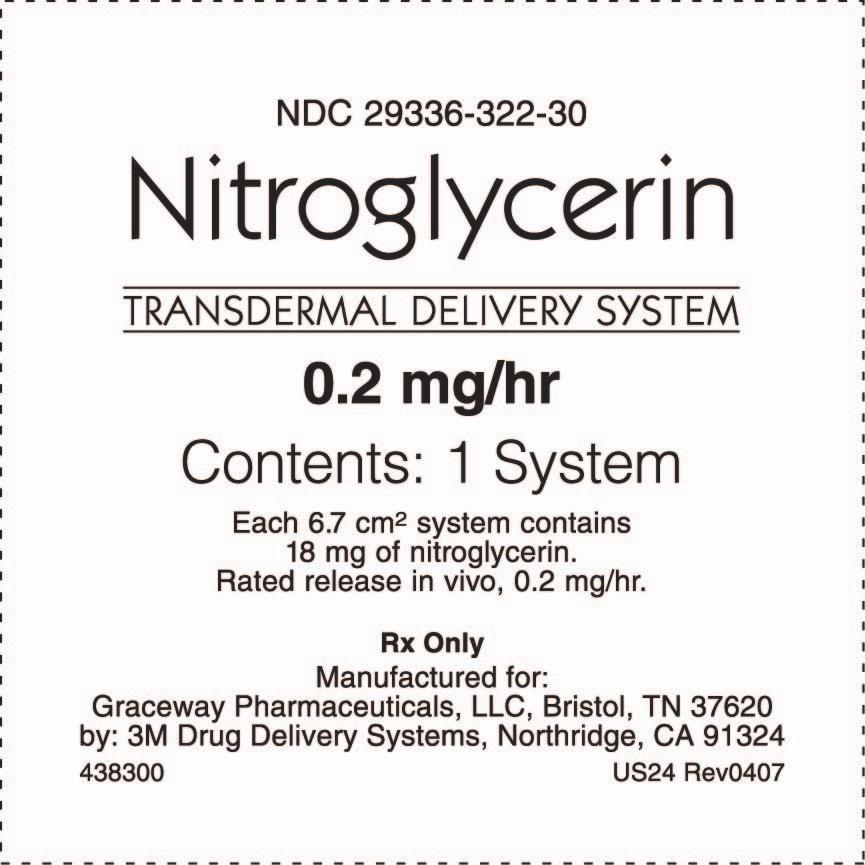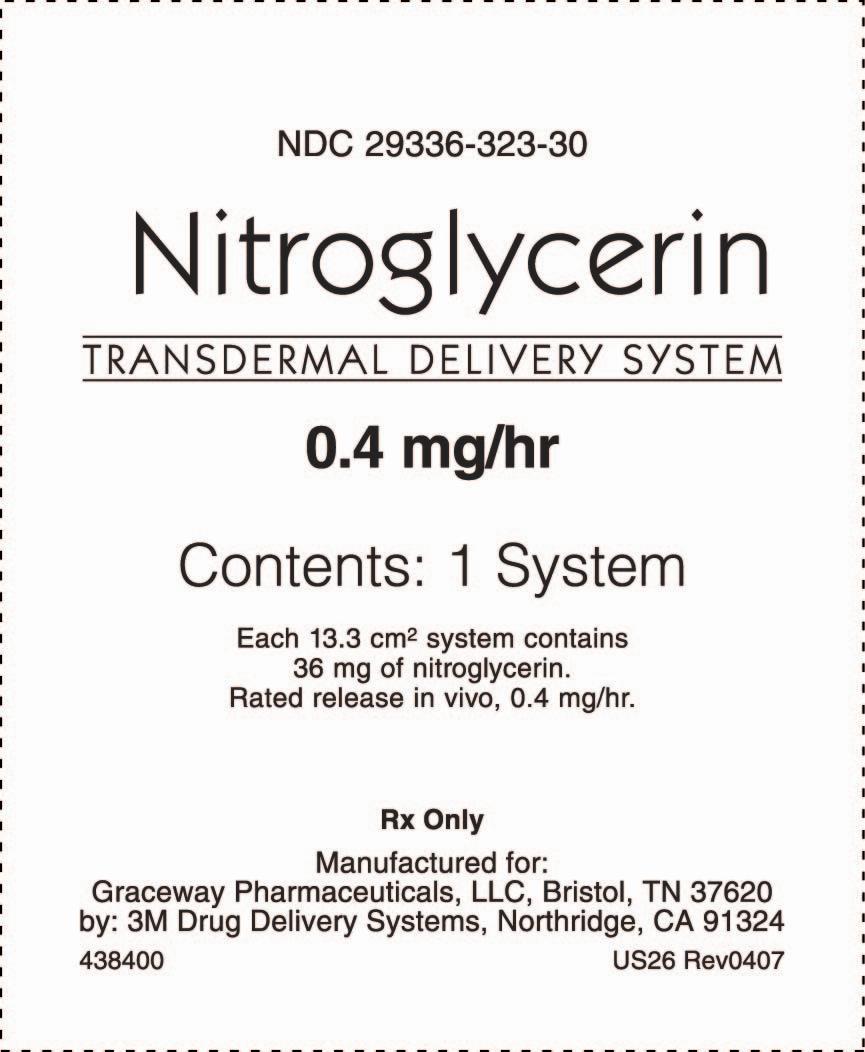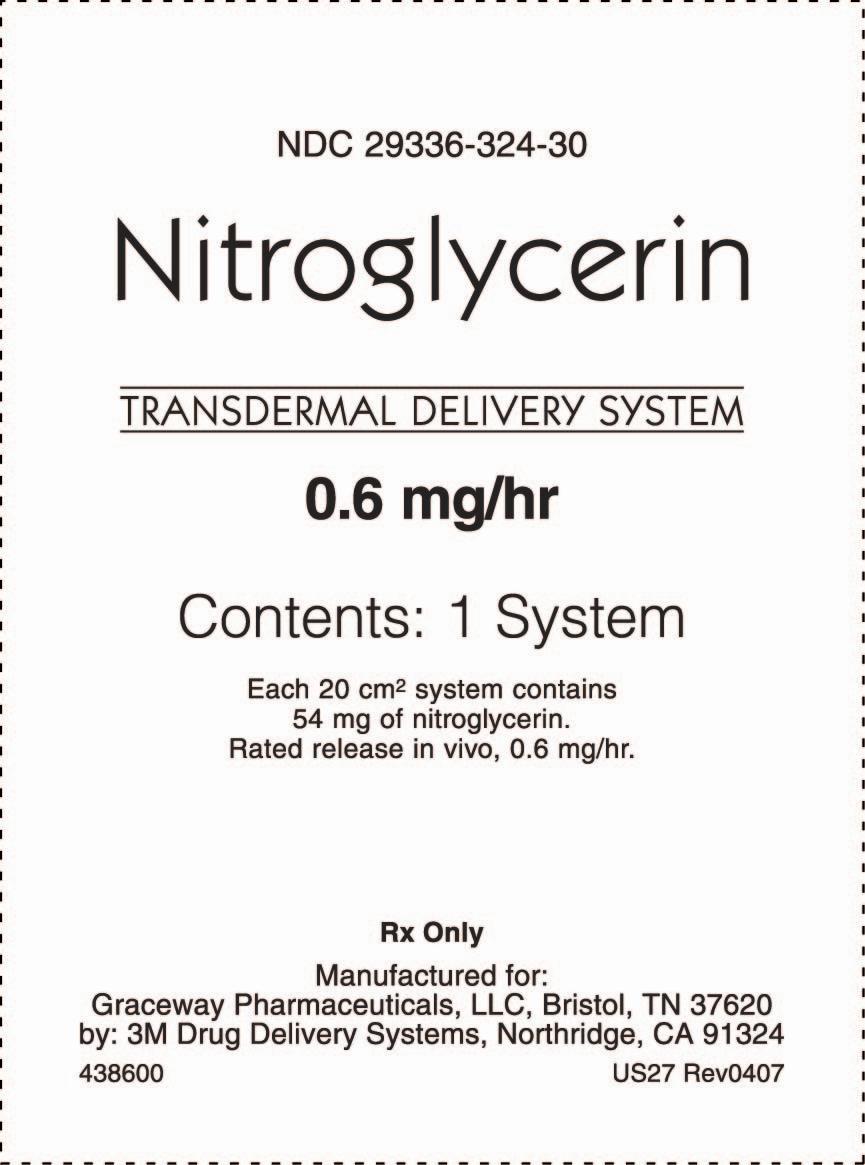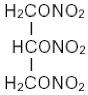 DRUG LABEL: Nitroglycerin Transdermal Delivery System 
NDC: 29336-321 | Form: PATCH
Manufacturer: Graceway Pharmaceuticals, LLC
Category: prescription | Type: HUMAN PRESCRIPTION DRUG LABEL
Date: 20091118

ACTIVE INGREDIENTS: nitroglycerin 2.5 mg/1 d

DESCRIPTION

Nitroglycerin is a 1,2,3-propanetriol trinitrate, an organic nitrate whose structural formula is

and whose molecular weight is 227.09. The organic nitrates are vasodilators, active on both arteries and veins.

The Nitroglycerin Transdermal Delivery System is a unit designed to provide continuous controlled release of nitroglycerin through intact skin. The rate of release of nitroglycerin is linearly dependent upon the area of the applied system; each cm^2 of applied system delivers approximately 0.03 mg of nitroglycerin per hour. Thus, the 3.3, 6.7, 13.3 and 20 cm^2 system delivers approximately 0.1, 0.2, 0.4 and 0.6 mg of nitroglycerin per hour, respectively.

The remainder of the nitroglycerin in each system serves as a reservoir and is not delivered in normal use. After 12 hours, for example, each system has delivered about 14% of its original content of nitroglycerin.

The Nitroglycerin Transdermal Delivery System contains nitroglycerin as the active component. The remaining components of the system (acrylate copolymer adhesive, fatty acid esters, and polyethylene backing) are pharmacologically inactive. Each patch is packaged in foil/polymer film laminate.

Prior to use, a protective peel strip is removed from the adhesive surface. Following use, the patch should be discarded in a manner that prevents accidental application or ingestion by children or others.

CLINICAL PHARMACOLOGY

The principal pharmacological action of nitroglycerin is relaxation of the vascular smooth muscle and consequent dilatation of peripheral arteries and veins, especially the latter. Dilatation of the veins promotes peripheral pooling of blood and decreases venous return to the heart, thereby reducing left ventricular end-diastolic pressure and pulmonary capillary wedge pressure (preload). Arteriolar relaxation reduces systemic vascular resistance, systolic arterial pressure, and mean arterial pressure (afterload). Dilatation of the coronary arteries also occurs. The relative importance of preload reduction, afterload reduction, and coronary dilatation remains undefined.

Dosing regimens for most chronically used drugs are designed to provide plasma concentrations that are continuously greater than a minimally effective concentration. This strategy is inappropriate for organic nitrates. Several well-controlled clinical trials have used exercise testing to assess the anti-anginal efficacy of continuously-delivered nitrates. In the large majority of these trials, active agents were indistinguishable from placebo after 24 hours (or less) of continuous therapy. Attempts to overcome nitrate tolerance by dose escalation, even to doses far in excess of those used acutely, have consistently failed. Only after nitrates have been absent from the body for several hours was their anti-anginal efficacy restored.

Pharmacokinetics:

The volume of distribution of nitroglycerin is about 3 L/kg, and nitroglycerin is cleared from this volume at extremely rapid rates, with a resulting serum half-life of about 3 minutes. The observed clearance rates (close to 1 L/kg/min) greatly exceed hepatic blood flow; known sites of extrahepatic metabolism include red blood cells and vascular walls.

The first products in the metabolism of nitroglycerin are inorganic nitrate and the 1,2- and 1,3-dinitroglycerols. The dinitrates are less effective vasodilators than nitroglycerin, but they are longer-lived in the serum, and their net contribution to the overall effect of chronic nitroglycerin regimens is not known.The dinitrates are further metabolized to (non-vasoactive) mononitrates and, ultimately, to glycerol and carbon dioxide.

To avoid development of tolerance to nitroglycerin, drug-free intervals of 10-12 hours are known to be sufficient; shorter intervals have not been well studied. In one well-controlled clinical trial, subjects receiving nitroglycerin appeared to exhibit a rebound or withdrawal effect, so that their exercise tolerance at the end of the daily drug-free interval was less than that exhibited by the parallel group receiving placebo.

In healthy volunteers, steady-state plasma concentrations of nitroglycerin are reached by about two hours after application of a patch and are maintained for the duration of wearing the system (observations have been limited to 24 hours). Upon removal of the patch, the plasma concentration declines with a half-life of about an hour.

Clinical Trials:

Regimens in which nitroglycerin patches were worn for 12 hours daily have been studied in well-controlled trials up to 4 weeks in duration. Starting about 2 hours after application and continuing until 10-12 hours after application, patches that deliver at least 0.4 mg of nitroglycerin per hour have consistently demonstrated greater anti-anginal activity than placebo. Lower-dose patches have not been as well studied, but in one large, well-controlled trial in which higher-dose patches were also studied, patches delivering 0.2 mg/hr had significantly less anti-anginal activity than placebo.

It is reasonable to believe that the rate of nitroglycerin absorption from patches may vary with the site of application, but this relationship has not been adequately studied.

The onset action of transdermal nitroglycerin is not sufficiently rapid for this product to be useful in aborting an acute anginal episode.

INDICATIONS AND USAGE

Transdermal nitroglycerin is indicated for the prevention of angina pectoris due to coronary artery disease. The onset of action of transdermal nitroglycerin is not sufficiently rapid for this product to be useful in aborting an acute attack.

CONTRAINDICATIONS

Allergic reactions to organic nitrates are extremely rare, but they do occur. Nitroglycerin is contraindicated in patients who are allergic to it. Allergy to the adhesives used in nitroglycerin patches has also been reported, and it similarly constitutes a contraindication to the use of this product.

WARNINGS

Amplification of the vasodilatory effects of Nitroglycerin Transdermal Delivery System by sildenafil can result in severe hypotension. The time course and dose dependence of this interaction have not been studied. Appropriate supportive care has not been studied, but it seems reasonable to treat this as a nitrate overdose, with elevation of the extremities and with central volume expansion.

The benefits of transdermal nitroglycerin in patients with acute myocardial infarction or congestive heart failure have not been established. If one elects to use nitroglycerin in these conditions, careful clinical or hemodynamic monitoring must be used to avoid the hazards of hypotension and tachycardia.

A cardiovertor/defibrillator should not be discharged through a paddle electrode that overlies a Nitroglycerin Transdermal Delivery System patch. The arcing that may be seen in this situation is harmless in itself, but it may be associated with local current concentration that can cause damage to the paddles and burns to the patient.

PRECAUTIONS

General:

Severe hypotension, particularly with upright posture, may occur with even small doses of nitroglycerin. This drug should therefore be used with caution in patients who may be volume depleted or who, for whatever reason, are already hypotensive. Hypotension induced by nitroglycerin may be accompanied by paradoxical bradycardia and increased angina pectoris.

Nitrate therapy may aggravate the angina caused by hypertrophic cardiomyopathy.

As tolerance to other forms of nitroglycerin develops, the effect of sublingual nitroglycerin on exercise tolerance, although still observable, is somewhat blunted.

In industrial workers who have had long-term exposure to unknown (presumably high) doses of organic nitrates, tolerance clearly occurs. Chest pain, acute myocardial infarction, and even sudden death have occurred during temporary withdrawal of nitrates from these workers, demonstrating the existence of true physical dependence.

Several clinical trials in patients with angina pectoris have evaluated nitroglycerin regimens which incorporated a 10-12 hour nitrate-free interval. In some of these trials, an increase in the frequency of anginal attacks during the nitrate-free interval was observed in a small number of patients. In one trial, patients demonstrated decreased exercise tolerance at the end of the nitrate-free interval. Hemodynamic rebound has been observed only rarely; on the other hand, few studies were so designed that rebound, if it had occurred, would have been detected. The importance of these observations to the routine, clinical use of transdermal nitroglycerin is unknown.

Information for Patients:

Daily headaches sometimes accompany treatment with nitroglycerin. In patients who get these headaches, the headache may be a marker of the activity of the drug. Patients should resist the temptation to avoid headaches by altering the schedule of their treatment with nitroglycerin, since loss of headache may be associated with simultaneous loss of anti-anginal efficacy.

Treatment with nitroglycerin may be associated with lightheadedness on standing, especially just after rising from a recumbent or seated position. This effect may be more frequent in patients who have also consumed alcohol.

After normal use, there is enough residual nitroglycerin in discarded patches that they are a potential hazard to children and pets.

A patient leaflet is supplied with the systems.

Drug Interactions:

The vasodilating effects of nitroglycerin may be additive with those of other vasodilators. Alcohol, in particular, has been found to exhibit additive effects of this variety.

Marked symptomatic orthostatic hypotension has been reported when calcium channel blockers and organic nitrates were used in combination. Dose adjustments of either class of agents may be necessary.

Carcinogenesis, Mutagenesis, and Impairment of Fertility:

Animal carcinogenesis studies with topically applied nitroglycerin have not been performed.

Rats receiving up to 434 mg/kg/day of dietary nitroglycerin for 2 years developed dose related fibrotic and neoplastic changes in liver, including carcinomas, and interstitial cell tumors in testes. At high dose, the incidences of hepatocellular carcinomas in both sexes were 52% vs 0% in controls, and incidences of testicular tumors were 52% vs 8% in controls. Incidences of pituitary adenomas and female mammary tumors normally seen in aged rats were significantly reduced, consistent with treatment-related decrease in food intake and body weight; increased life span was also seen in the high-dose females. Lifetime dietary administration of up to 1058 mg/kg/day of nitroglycerin was not tumorigenic in mice.

Nitroglycerin was weakly mutagenic in Ames tests performed in two different laboratories. Nevertheless, there was no evidence of mutagenicity in an in vivo dominant lethal assay with male rats treated with doses up to about 363 mg/kg/day, p.o., or in vitro cytogenetic tests in rat and dog tissues.

In a three-generation reproduction study, rats received dietary nitroglycerin at doses up to about 434 mg/kg/day for 6 months prior to mating of the F0 generation with treatment continuing through successive F1 and F2 generations. The high dose was associated with decreased feed intake and body weight gain in both sexes at all matings. No specific effect on the fertility of the F0 generation was seen. Infertility noted in subsequent generations, however, was attributed to increased interstitial cell tissue and aspermatogenesis in the high-dose males. In this three-generation study there was no clear evidence of teratogenicity.

Pregnancy Category C:

Animal teratology studies have not been conducted with nitroglycerin transdermal systems. Teratology studies in rats and rabbits, however, were conducted with topically applied nitroglycerin ointment at doses up to 80 mg/kg/day and 240 mg/kg/day, respectively. No toxic effects on dams or fetuses were seen at any dose tested. There are no adequate and well-controlled studies in pregnant women. Nitroglycerin should be given to a pregnant woman only if clearly needed.

Nursing Mothers:

It is not known whether nitroglycerin is excreted in human milk. Because many drugs are excreted in human milk, caution should be exercised when nitroglycerin is administered to a nursing woman.

Pediatric Use:

Safety and effectiveness in pediatric patients have not been established.

ADVERSE REACTIONS

Adverse reactions to nitroglycerin are generally dose-related, and almost all of these reactions are the result of nitroglycerin's activity as a vasodilator. Headache, which may be severe, is the most commonly reported side effect. Headache may be recurrent with each daily dose, especially at higher doses. Transient episodes of lightheadedness, occasionally related to blood pressure changes, may also occur. Hypotension occurs infrequently, but in some patients it may be severe enough to warrant discontinuation of therapy. Syncope, crescendo angina, and rebound hypertension have been reported but are uncommon.

Extremely rarely, ordinary doses of organic nitrates have caused methemoglobinemia in normal-seeming patients. Methemoglobinemia is so infrequent at these doses that further discussion of its diagnosis and treatment is deferred (see OVERDOSAGE).

Allergic reactions to nitroglycerin are also uncommon, and the great majority of those reported have been cases of contact dermatitis or fixed drug eruptions in patients receiving nitroglycerin in ointments or patches. There have been a few reports of genuine anaphylactoid reactions, and these reactions can probably occur in patients receiving nitroglycerin by any route.

In two placebo-controlled trials of intermittent therapy with nitroglycerin patches at 0.2 to 0.8 mg/hr, the most frequent adverse reactions among 307 subjects were as follows:

 | placebo | patch
headache | 18% | 63%
lightheadedness | 4% | 6%
hypotension and/or syncope | 0% | 4%
increased angina | 2% | 2%

OVERDOSAGE

Hemodynamic Effects:

The ill effects of nitroglycerin overdose are generally the results of nitroglycerin's capacity to induce vasodilatation, venous pooling, reduced cardiac output, and hypotension. These hemodynamic changes may have protean manifestations, including increased intracranial pressure, with any or all of persistent throbbing headache, confusion, and moderate fever; vertigo; palpitations; visual disturbances; nausea and vomiting (possibly with colic and even bloody diarrhea); syncope (especially in the upright posture); air hunger and dyspnea, later followed by reduced ventilatory effort; diaphoresis, with the skin either flushed or cold and clammy; heart block and bradycardia; paralysis; coma; seizures; and death.

Laboratory determinations of serum levels of nitroglycerin and its metabolites are not widely available, and such determinations have, in any event, no established role in the management of nitroglycerin overdose.

No data are available to suggest physiological maneuvers (e.g., maneuvers to change the pH of the urine) that might accelerate elimination of nitroglycerin and its active metabolites. Similarly, it is not known which – if any – of these substances can usefully be removed from the body by hemodialysis.

No specific antagonist to the vasodilator effects of nitroglycerin is known, and no intervention has been subject to controlled study as a therapy of nitroglycerin overdose. Because the hypotension associated with nitroglycerin overdose is the result of venodilatation and arterial hypovolemia, prudent therapy in this situation should be directed toward an increase in central fluid volume. Passive elevation of the patient's legs may be sufficient, but intravenous infusion of normal saline or similar fluid may also be necessary.

The use of epinephrine or other arterial vasoconstrictors in this setting is likely to do more harm than good.

In patients with renal disease or congestive heart failure, therapy resulting in central volume expansion is not without hazard. Treatment of nitroglycerin overdose in these patients may be subtle and difficult, and invasive monitoring may be required.

Methemoglobinemia:

Nitrate ions liberated during metabolism of nitroglycerin can oxidize hemoglobin into methemoglobin. Even in patients totally without cytochrome b5 reductase activity, however, and even assuming that nitrate moieties of nitroglycerin are quantitatively applied to oxidation of hemoglobin, about 1 mg/kg of nitroglycerin should be required before any of these patients manifests clinically significant (≥10%) methemoglobinemia. In patients with normal reductase function, significant production of methemoglobin should require even larger doses of nitroglycerin. In one study in which 36 patients received 2-4 weeks of continuous nitroglycerin therapy at 3.1 to 4 mg/hr, the average methemoglobin level measured was 0.2%; this was comparable to that observed in parallel patients who received placebo.

Notwithstanding these observations, there are case reports of significant methemoglobinemia in association with moderate overdoses of organic nitrates. None of the affected patients had been thought to be unusually susceptible.

Methemoglobin levels are available from most clinical laboratories. The diagnosis should be suspected in patients who exhibit signs of impaired oxygen delivery despite adequate cardiac output and adequate arterial pO2. Classically, methemoglobinemic blood is described as chocolate brown, without color change on exposure to air.

When methemoglobinemia is diagnosed, the treatment of choice is methylene blue, 1 to 2 mg/kg intravenously.

DOSAGE AND ADMINISTRATION

The suggested starting dose is between 0.2 mg/hr and 0.4 mg/hr. Doses between 0.4 mg/hr and 0.8 mg/hr have shown continued effectiveness for 10-12 hours daily for at least one month (the longest period studied) of intermittent administration. Although the minimum nitrate-free interval has not been defined, data show that a nitrate-free interval of 10-12 hours is sufficient (see CLINICAL PHARMACOLOGY). Thus, an appropriate dosing schedule for nitroglycerin patches would include a daily patch-on period of 12-14 hours and a daily patch-off period of 10-12 hours.

Although some well-controlled clinical trials using exercise tolerance testing have shown maintenance of effectiveness when patches are worn continuously, the large majority of such controlled trials have shown the development of tolerance (i.e., complete loss of effect) within the first 24 hours after therapy was initiated. Dose adjustment, even to levels much higher than generally used, did not restore efficacy.

PATIENT INSTRUCTIONS FOR APPLICATION OF SYSTEM

A patient leaflet is supplied with each carton.

HOW SUPPLIED

Nitroglycerin Transdermal Delivery System Rated Release In Vivo | System Size | Total Nitro- glycerin In System | NDC Number
0.1 mg/hr | 3.3 cm^2 | 9 mg | NDC-29336-321-30
0.2 mg/hr | 6.7 cm^2 | 18 mg | NDC-29336-322-30
0.4 mg/hr | 13.3 cm^2 | 36 mg | NDC-29336-323-30
0.6 mg/hr | 20.0 cm^2 | 54 mg | NDC-29336-324-30

Nitroglycerin Transdermal Delivery System, 0.1 mg/hr, 0.2 mg/hr, 0.4 mg/hr, 0.6 mg/hr is available in cartons of 30 patches.

STORAGE CONDITIONS

Store at controlled room temperature 15°-30°C (59°-86°F). Extremes of temperature and/or humidity should be avoided.

Rx only

US30 Rev. 4-07

Manufactured for:
Graceway Pharmaceuticals, LLC
Bristol, TN 37620

by:
3M Drug Delivery Systems
Northridge, CA 91324

PACKAGE LABEL.PRINCIPAL DISPLAY PANEL

NDC 29336-321-30
Nitroglycerin
Transdermal Delivery System
0.1 mg/hr
Contents: 1 System
Each 3.3 cm^2 sytem contains 9 mg of nitroglycerin.
Rated release in vivo, 0.1 mg/hr.
Rx Only
Manufactured for:
Graceway Pharmaceuticals, LLC, Bristol, TN 37620
by: 3M Drug Delivery Systems, Northridge, CA 91324
438200 US23 Rev0407

NDC 29336-322-30
Nitroglycerin
Transdermal Delivery System
0.2 mg/hr
Contents: 1 System
Each 6.7 cm^2 sytem contains 18 mg of nitroglycerin.
Rated release in vivo, 0.2 mg/hr.
Rx Only
Manufactured for:
Graceway Pharmaceuticals, LLC, Bristol, TN 37620
by: 3M Drug Delivery Systems, Northridge, CA 91324
438300 US24 Rev0407

NDC 29336-323-30
Nitroglycerin
Transdermal Delivery System
0.4 mg/hr
Contents: 1 System
Each 13.3 cm^2 sytem contains 36 mg of nitroglycerin.
Rated release in vivo, 0.4 mg/hr.
Rx Only
Manufactured for:
Graceway Pharmaceuticals, LLC, Bristol, TN 37620
by: 3M Drug Delivery Systems, Northridge, CA 91324
438400 US26 Rev0407

NDC 29336-324-30
Nitroglycerin
Transdermal Delivery System
0.6 mg/hr
Contents: 1 System
Each 20 cm^2 sytem contains 54 mg of nitroglycerin.
Rated release in vivo, 0.6 mg/hr.
Rx Only
Manufactured for:
Graceway Pharmaceuticals, LLC, Bristol, TN 37620
by: 3M Drug Delivery Systems, Northridge, CA 91324
438600 US27 Rev0407